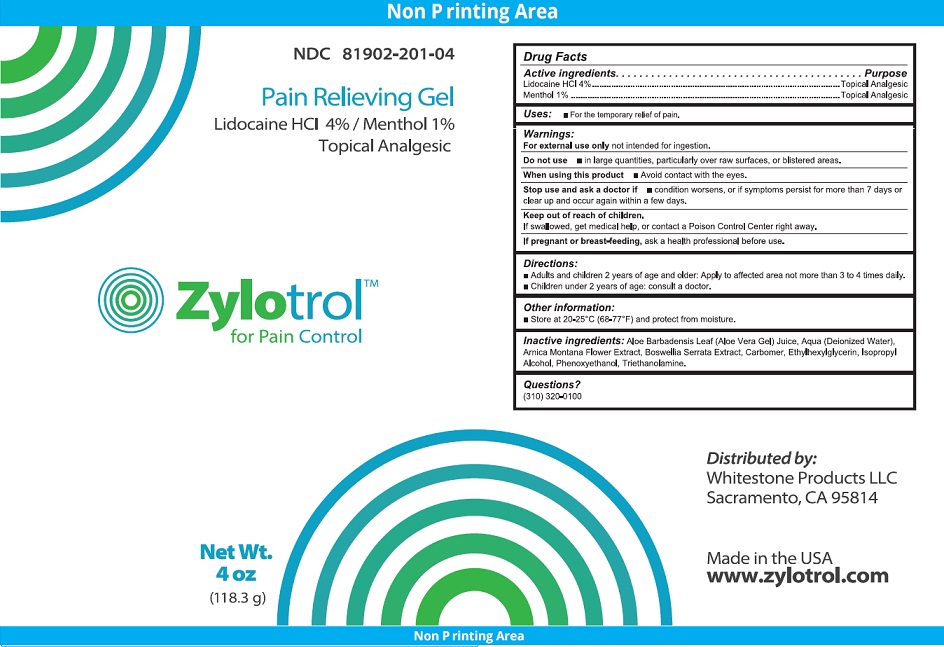 DRUG LABEL: Zylotrol
NDC: 81902-201 | Form: GEL
Manufacturer: Whitestone Products LLC
Category: otc | Type: HUMAN OTC DRUG LABEL
Date: 20231016

ACTIVE INGREDIENTS: LIDOCAINE HYDROCHLORIDE 4 g/100 g; MENTHOL, UNSPECIFIED FORM 1 g/100 g
INACTIVE INGREDIENTS: ALOE VERA LEAF; WATER; ARNICA MONTANA FLOWER; INDIAN FRANKINCENSE; CARBOMER HOMOPOLYMER, UNSPECIFIED TYPE; ETHYLHEXYLGLYCERIN; ISOPROPYL ALCOHOL; PHENOXYETHANOL; TROLAMINE

Zylotrol

Active Ingredients

Lidocaine HCl 4%

Menthol 1%

Purpose

Topical Analgesic

Uses

For the temporary relief of pain.

Warnings

For external use only not intended for ingestion.

Do not use

- in large quantities, particularly over raw surfaces, or blistered areas.

When using this product

- Avoid contact with the eyes.

Stop use and ask a doctor if

- condition worsens, or if symtoms persist for more than 7 days or clear up and occur again within a few days.

Keep out of reach of children.

If swallowed, get medical help, or contact a Poison Control Central right away.

PREGNANCY OR BREAST FEEDING

If pregnant or breast-feeding, ask a health professional before use.

Directions

- Adults and children 2 years of age and older: Apply to affected area not more than 3 to 4 times a daily.
- Children under 2 years of age: consult a doctor.

Other information

- Store at 20-25oC (68-77oF) and protect from moisture.

Inactive ingredients

Aloe Barbadensis Leaf (Aloe Vera Gel) Juice, Aqua (Deionized Water), Arnica Montana Flower Extract, Boswellia Serrata Extract, Carbomer, Ethylhexylglycerin, Isopropyl Alcohol, Phenoxyethanol, Triethanolamine.

Questions?

(310) 320-0100